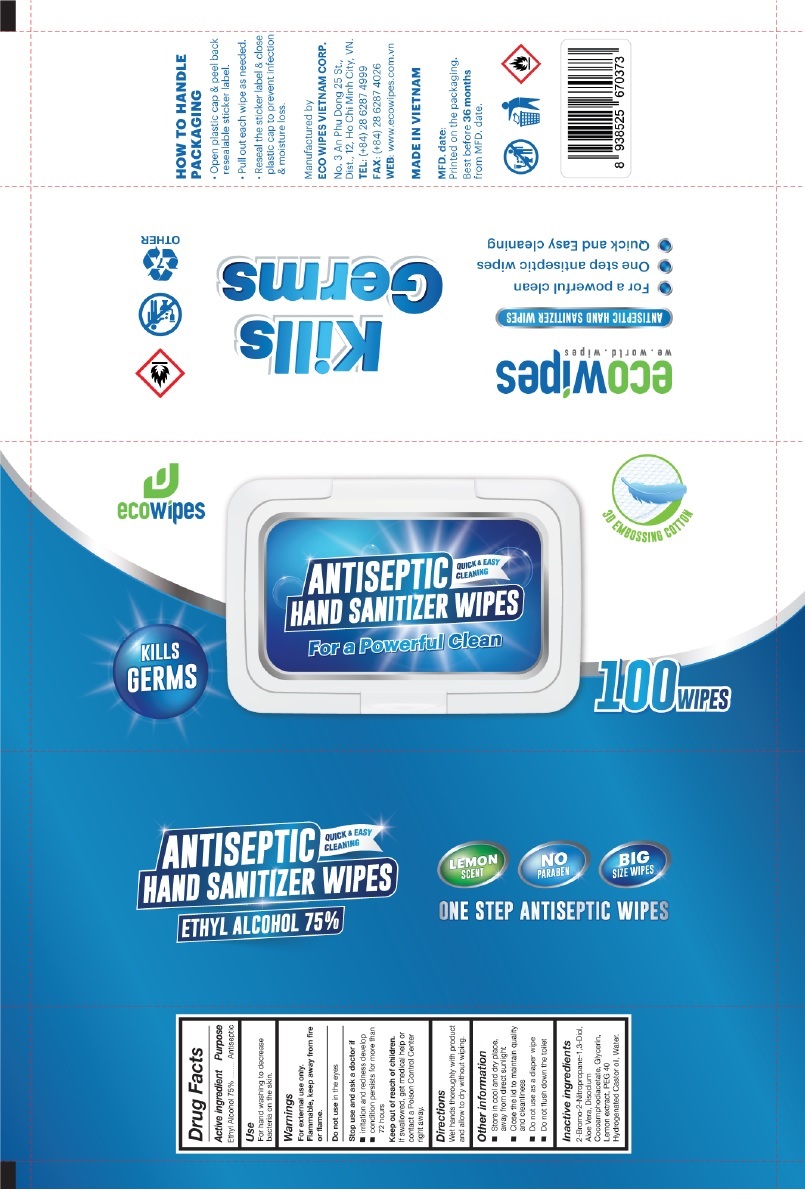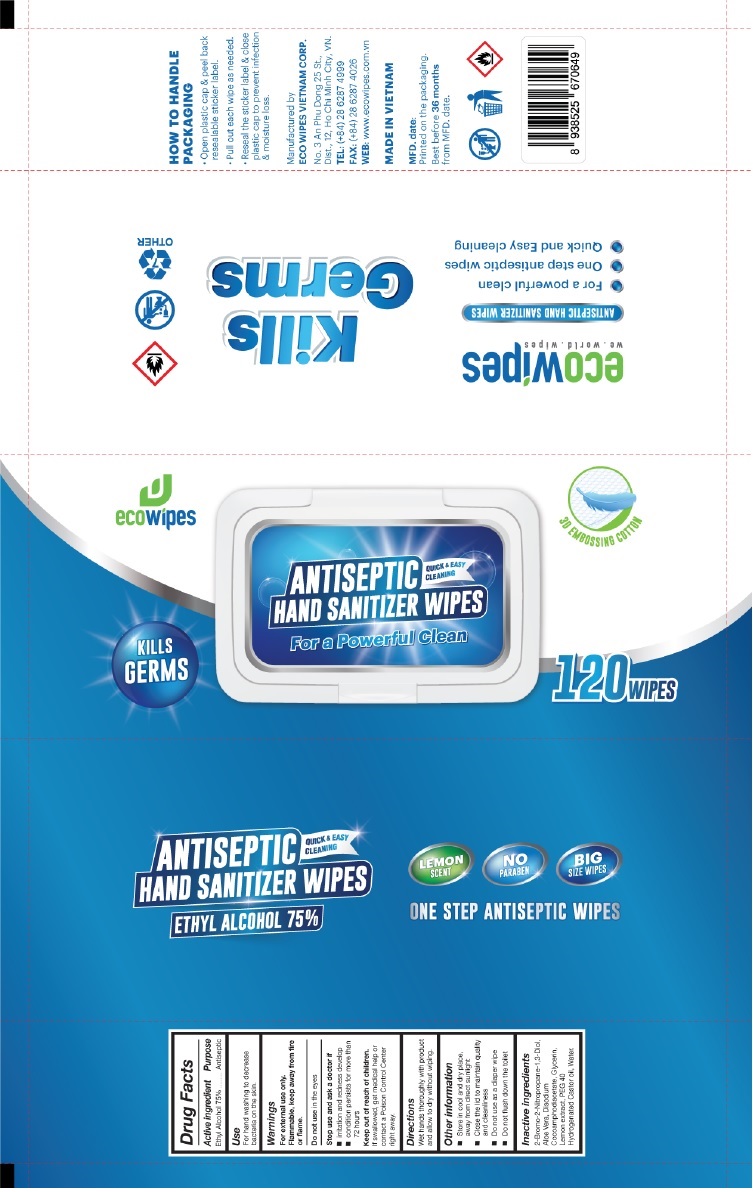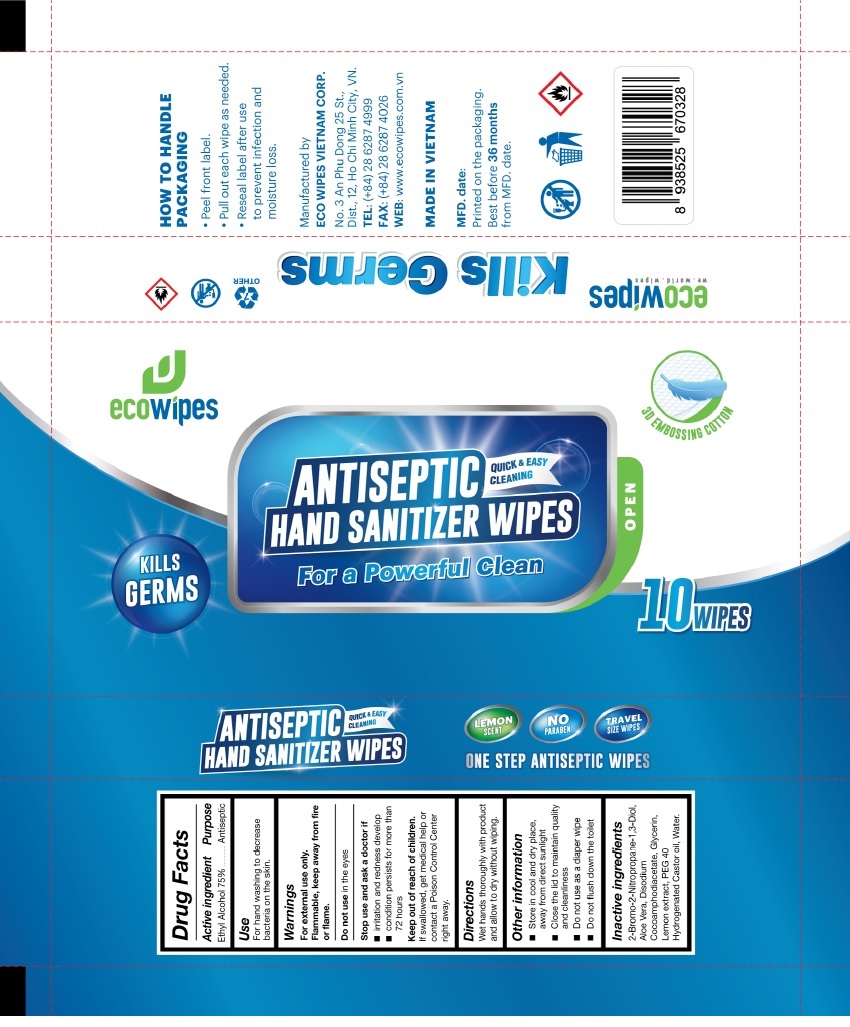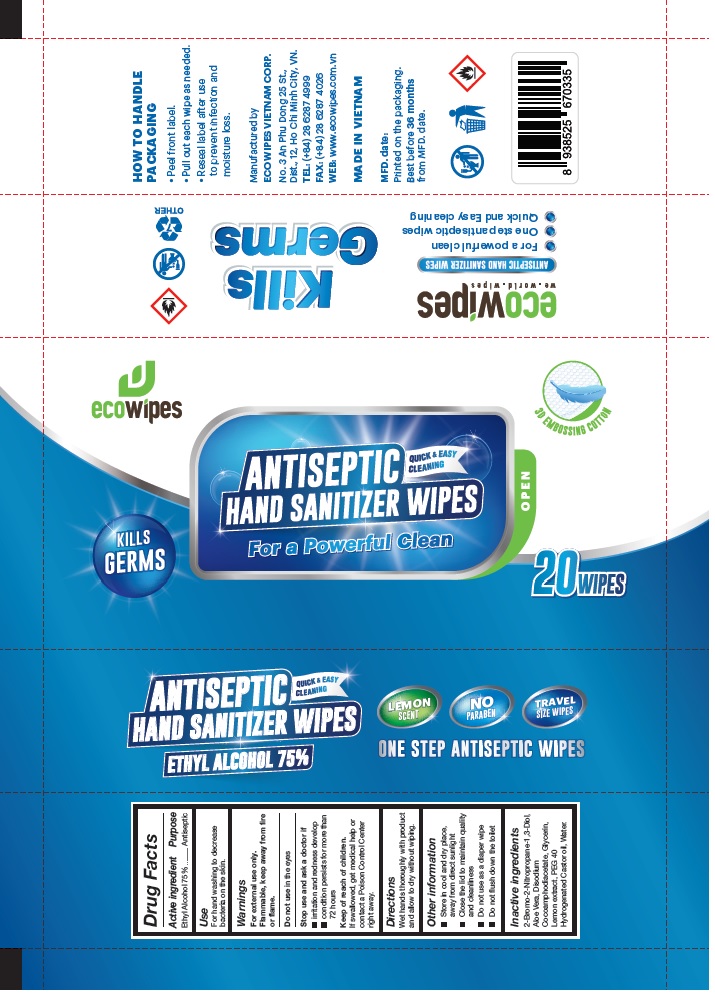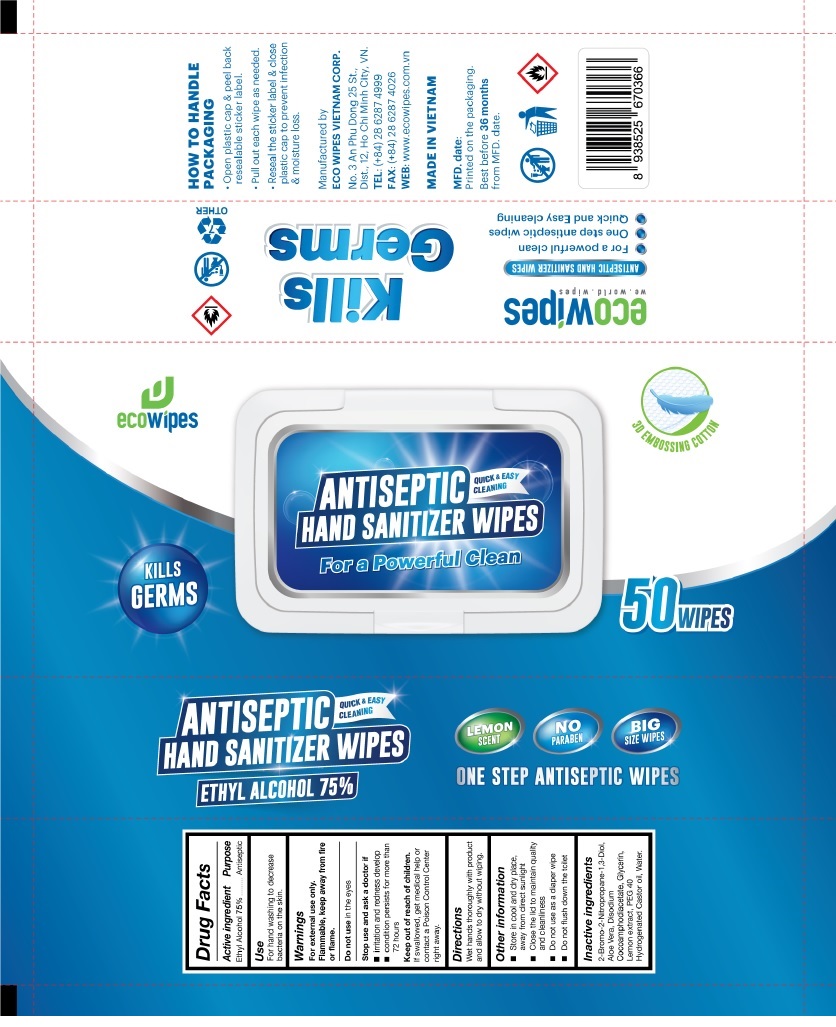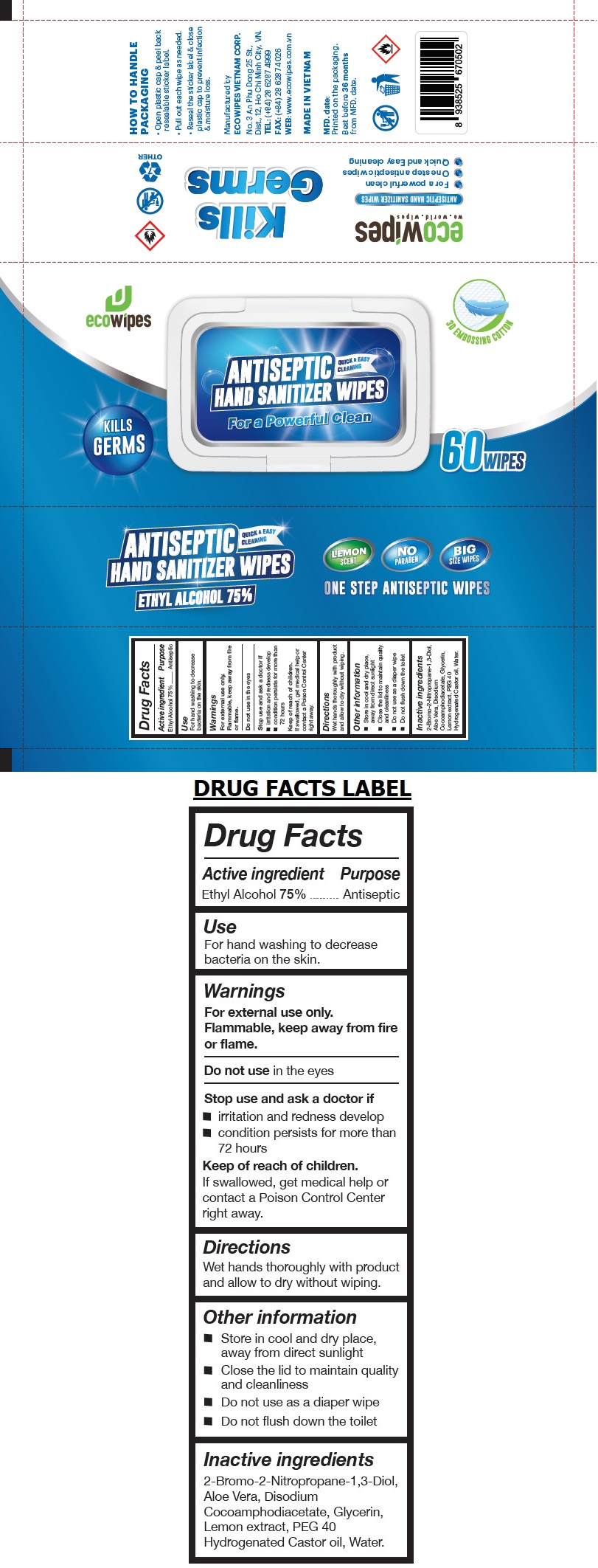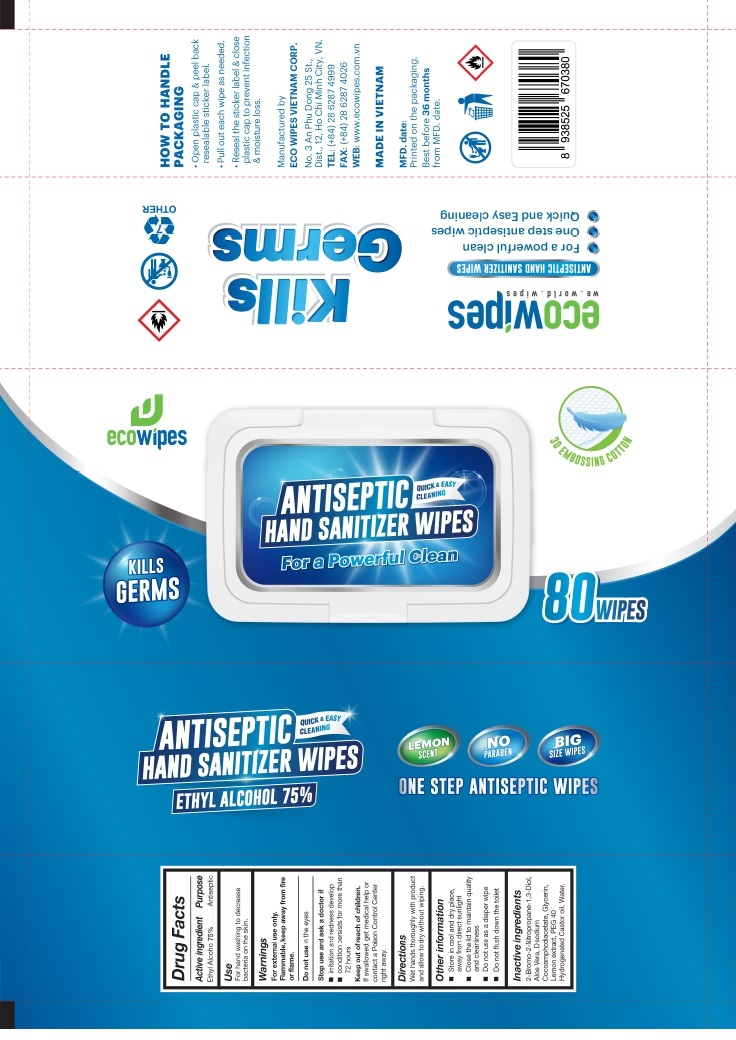 DRUG LABEL: ECOWIPES ANTISEPTIC HAND SANITIZER WIPES
NDC: 78898-275 | Form: CLOTH
Manufacturer: Eco Wipes Vietnam Corporation
Category: otc | Type: HUMAN OTC DRUG LABEL
Date: 20200806

ACTIVE INGREDIENTS: ALCOHOL 0.75 g/1 mL
INACTIVE INGREDIENTS: BRONOPOL; ALOE VERA LEAF; DISODIUM COCOAMPHODIACETATE; GLYCERIN; LEMON; POLYOXYL 40 HYDROGENATED CASTOR OIL; WATER

ecowipes ANTISEPTIC HAND SANITIZER WIPES

Active ingredient

Ethyl Alcohol 75%

Purpose

Antiseptic

Use

For hand washing to decrease bacteria on the skin.

Warnings

For external use only.

Flammable, keep away from fire or flame.

Do not use in the eyes

Stop use and ask a doctor if

▪ irritation and redness develop

▪ condition persists for more than 72 hours

Keep out of reach of children.

If swallowed, get medical help or contact a Poison Control Center right away.

Directions

Wet hands thoroughly with product and allow to dry without wiping.

Other information

▪ Store in cool and dry place, away from direct sunlight

▪ Close the lid to maintain quality and cleanliness

▪ Do not use as a diaper wipe

▪ Do not flush down the toilet

Inactive ingredients

2-Bromo-2-Nitropropane-1,3-Diol, Aloe Vera, Disodium Cocoamphodiacetate, Glycerin, Lemon extract, PEG 40 Hydrogenated Castor oil, Water.

QUICK & EASY CLEANING

For a Powerful Clean

KILLS GERMS

3D EMBOSSING COTTON

LEMON SCENT

NO PARABEN

BIG SIZE WIPES

ONE STEP ANTISEPTIC WIPES

we ▪ world ▪ wipes

ANTISEPTIC HAND SANITIZER WIPES

- For a powerful clean
- One step antiseptic wipes
- Quick and easy cleaning

HOW TO HANDLE PACKAGING

- Peel front label.
- Pull out each wipe as needed.
- Reseal label after use to prevent infection and moisture loss.

HOW TO HANDLE PACKAGING

- Open plastic cap & peel back resealable sticker label.
- Pull out each wipe as needed.
- Reseal the sticker label & close plastic cap to prevent infection & moisture loss.

Manufactured by

ECO WIPES VIETNAM CORP.

No. 3 An Phu Dong 25 St.,

Dist., 12, Ho Chi Minh City, VN.

TEL: (+84) 28 6287 4999

FAX: (+84) 28 6287 4026

WEB: www.ecowipes.com.vn

MADE IN VIETNAM

Best before 36 months from MFD. date.